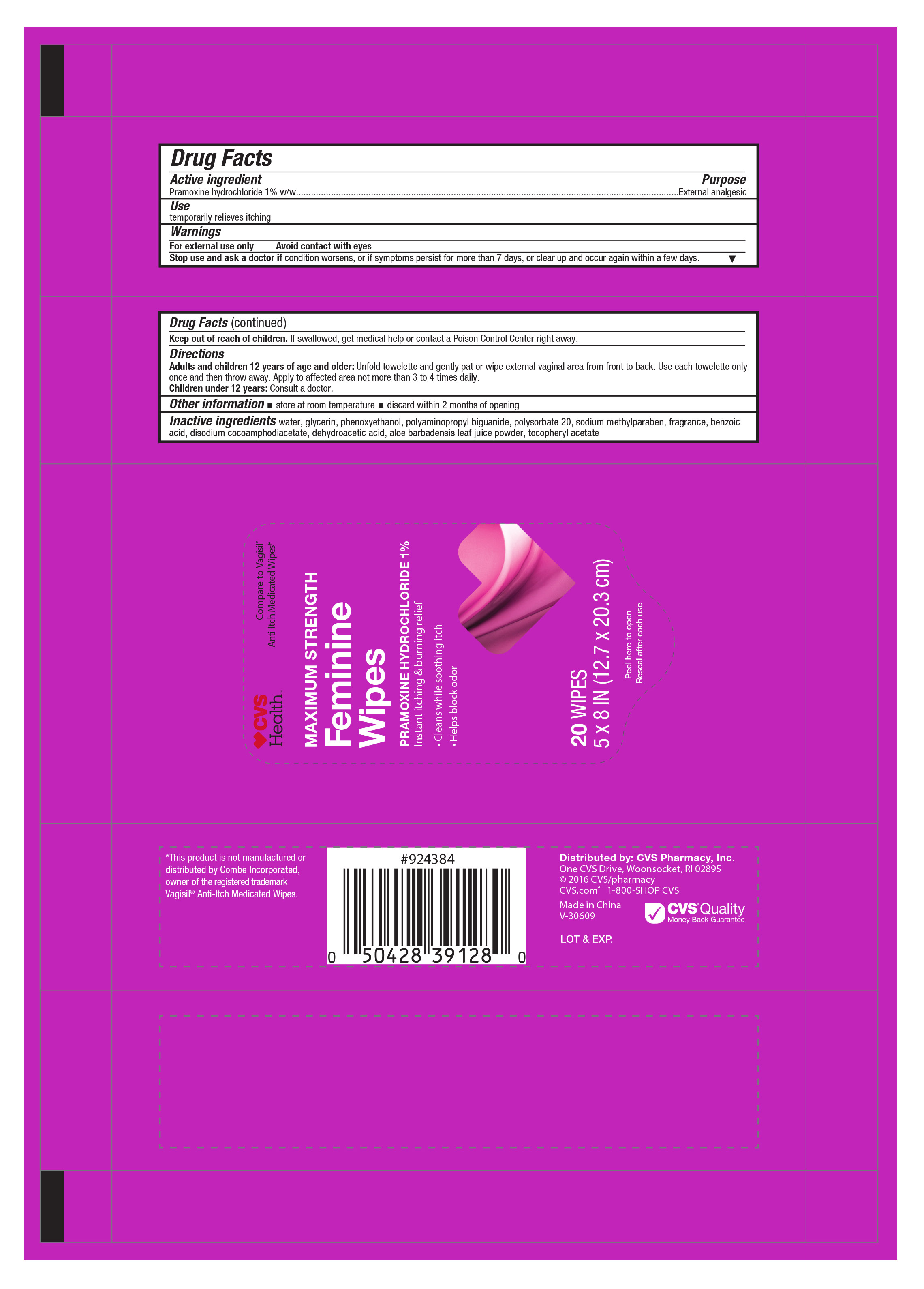 DRUG LABEL: CVS Health Maximum Strength Feminine
NDC: 69842-128 | Form: CLOTH
Manufacturer: CVS Pharmacy
Category: otc | Type: HUMAN OTC DRUG LABEL
Date: 20170127

ACTIVE INGREDIENTS: PRAMOXINE HYDROCHLORIDE 1 mg/1 1
INACTIVE INGREDIENTS: WATER; GLYCERIN; PHENOXYETHANOL; POLYSORBATE 20; SODIUM; METHYLPARABEN; BENZOIC ACID; DISODIUM COCOAMPHODIACETATE; DEHYDROACETIC ACID; ALOE VERA LEAF; .ALPHA.-TOCOPHEROL ACETATE

Active ingredient Purpose

Pramoxine hydrochloride 1% w/w......................................Extnernal analgesic

Use

temporarily relieves itching

Warnings

For external use only

Avoid contact with eyes

Keep out of reach of children. If swallowed, get medical help or contact a Poison Control Center right away.

Directions

Adults and children 12 years of age and older: Unfold towellete and gently pat or wipes external vaginal area from front to back. Use each towelette only once and then throw away. Apply to affected area not more than 3 to 4 times daily.

Children under 12 years of age: Consult a doctor.

Other information

- store at room temperature
- discard within 2 months of opening

Inactive ingredients

water, glycerin, phenoxyethanol, polyaminopropyl biguanide, polysorbate 20, sodium methylparaben, fragrance, benzoic acid, disodium cocamphodiacetate, dehydroacetic acid, aloe barbadensis leaf juice powder, toceopheryl acetate

DOSAGE AND ADMINISTRATION

Distributed by:

CVS Pharmacy, Inc.

Once CVS Drive,

Woonsocket, RI 02895

CVS.com 1-800-SHOP CVS

Made in China